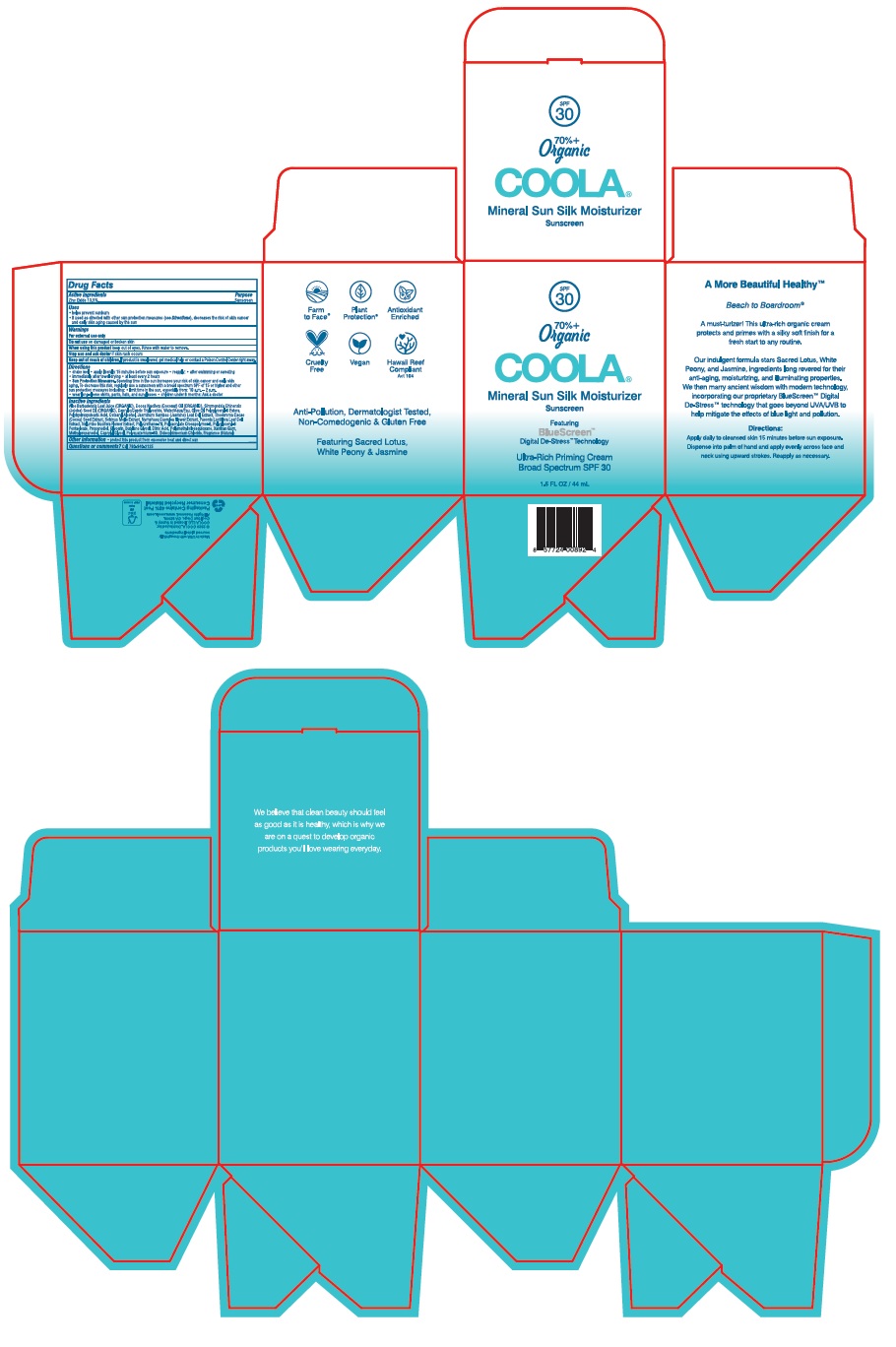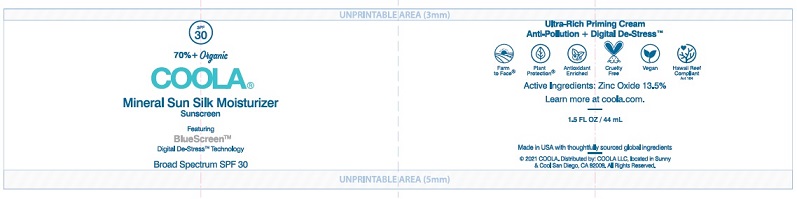 DRUG LABEL: Mineral Sun Silk Moisturizer Sunscreen
NDC: 79753-078 | Form: CREAM
Manufacturer: COOLA LLC
Category: otc | Type: HUMAN OTC DRUG LABEL
Date: 20230409

ACTIVE INGREDIENTS: ZINC OXIDE 135 mg/1 mL
INACTIVE INGREDIENTS: ALOE VERA LEAF; COCONUT OIL; JOJOBA OIL; MEDIUM-CHAIN TRIGLYCERIDES; WATER; OLIVE OIL POLYGLYCERYL-6 ESTERS; POLYHYDROXYSTEARIC ACID (2300 MW); CETOSTEARYL ALCOHOL; JASMINUM SAMBAC FLOWER; COCOA; SCHINUS MOLLE FRUITING TOP; NYMPHAEA CAERULEA FLOWER; PAEONIA LACTIFLORA FLOWER; NELUMBO NUCIFERA FLOWER; AMMONIUM ACRYLOYLDIMETHYLTAURATE, DIMETHYLACRYLAMIDE, LAURYL METHACRYLATE AND LAURETH-4 METHACRYLATE COPOLYMER, TRIMETHYLOLPROPANE TRIACRYLATE CROSSLINKED (45000 MPA.S); PROPANEDIOL; GLYCERIN; BUTYLENE GLYCOL; CITRIC ACID MONOHYDRATE; POLYMETHYLSILSESQUIOXANE (11 MICRONS); XANTHAN GUM; METHYLPROPANEDIOL; CAPRYLYL GLYCOL; POLYQUATERNIUM-80; DIDECYLDIMONIUM CHLORIDE

COOLA Mineral Sun Silk Moisturizer Sunscreen SPF 30

DRUG FACTS

Active ingredients

Zinc Oxide 13.5%

Purpose

Sunscreen

Warnings

For external use only

When using this product keep out of eyes. Rinse with water to remove

Stop use and ask doctor if skin rash occurs

Keep out of reach of children. If product is swallowed, get medical help or contact a Poison Control Center right away.

Directions

* shake well * apply liberally 15 minutes before sun exposure

* reapply: * after swimming or sweating * immediately after towel drying * at least every 2 hours

* Sun Protection Measures. Spending time in the sun increases your risk of skin cancer and early aging. To decrease this risk, regularly use a sunscreen with a broad spectrum SPF of 15 or higher and other sun protection measures including: * limit time in the sun, especially from: 10 a.m. – 2 p.m.

* wear long-sleeve shirts, pants, hats, and sunglasses

* children under 6 months: Ask a doctor

Inactive Ingredients
Aloe Barbadensis Leaf Juice (ORGANIC), Cocos Nucifera (Coconut) Oil (ORGANIC), Simmondsia Chinensis
(Jojoba) Seed Oil (ORGANIC), Caprylic/Capric Triglyceride, Water/Aqua/Eau, Olive Oil Polyglyceryl-6 Esters,
Polyhydroxystearic Acid, Cetearyl Alcohol, Jasminum Sambac (Jasmine) Leaf Cell Extract, Theobroma Cacao
(Cocoa) Seed Extract, Schinus Molle Extract, Nymphaea Caerulea Flower Extract, Paeonia Lactiflora Leaf Cell
Extract, Nelumbo Nucifera Flower Extract, Polyurethane-79, Polyacrylate Crosspolymer-6, Polyglyceryl-6
Pentaoleate, Propanediol, Glycerin, Butylene Glycol, Citric Acid, Polymethylsilsesquioxane, Xanthan Gum,
Methylpropanediol, Caprylyl Glycol, Polyquaternium-80, Didecyldimonium Chloride, Fragrance (Natural)

Other information

* protect this product from excessive heat and direct sun

QUESTIONS

Questionsor Comments? Call 760-940-2125

Package Labeling - COOLA Mineral Sun Silk Moisturizer Sunscreen SPF 30

SPF
30

70% +
Organic

COOLA

Mineral Sun Silk Moisturizer

Sunscreen

Ultra-Rich Priming Cream

Broad Spectrum SPF 30

1.5 FL OZ / 44 mL

2020 COOLA. Distributed by:

COOLA LLC, located in Sunny &

Cool San Diego, CA 92009.

All Rights Reserved. www.coola.com

Carton

Jar